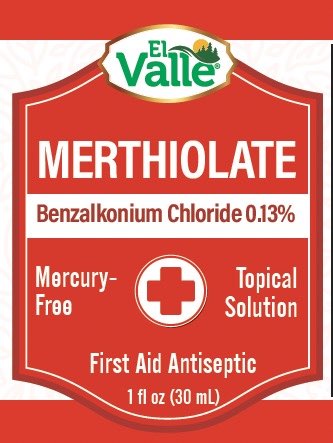 DRUG LABEL: El Valle Merthiolate
NDC: 55758-375 | Form: LIQUID
Manufacturer: Pharmadel LLC
Category: otc | Type: HUMAN OTC DRUG LABEL
Date: 20251204

ACTIVE INGREDIENTS: BENZALKONIUM CHLORIDE 1.3 mg/1 mL
INACTIVE INGREDIENTS: FD&C RED NO. 40; ALCOHOL; WATER

El Valle Merthiolate (Benz Chloride 0.13%)(DA)

Drug Facts

Active Ingredient & Purpose

Active ingredient | Purpose
Benzalkonium chloride 0.13%............. | First aid antiseptic

Uses

First aid to help prevent infection in

- minor cuts
- scrapes
- burns

Warnings

FOR EXTERNAL USE ONLY.

Do not use

- longer than 1 week, unless directed by a doctor
- in the eyes
- over large areas of the body

Ask a doctor before use if you have

- a deep or puncture wounds
- serious burns
- animal bites

Stop use and consult a doctor if

- conditions persist or gets worse

Keep out of reach of children.

If swallowed, get medical help, or contact a Poison Control Center immediately.

Directions

- clean the affected area
- apply a small amount directly to the affected area 1 to 3 times a day
- may cover area with a sterile bandage

Other information

- do not use if clear seal over cap is missing or broken

Inactive ingredients

alcohol, FD&C red #40, water